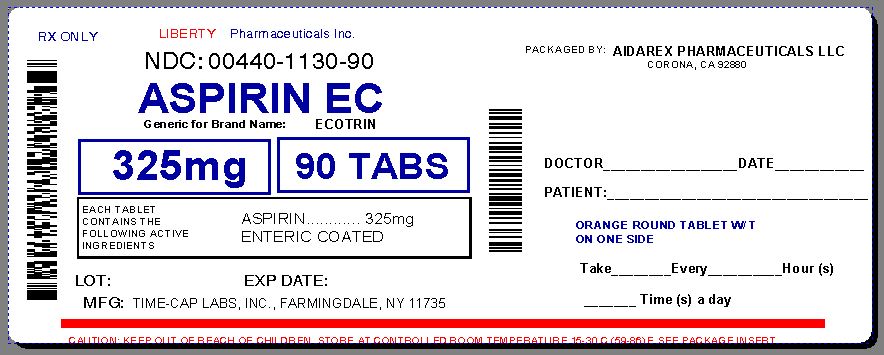 DRUG LABEL: ASPIRIN
NDC: 0440-1130 | Form: TABLET, COATED
Manufacturer: Liberty Pharmaceuticals, Inc.
Category: otc | Type: HUMAN OTC DRUG LABEL
Date: 20130905

ACTIVE INGREDIENTS: ASPIRIN 325 ng/1 1
INACTIVE INGREDIENTS: STARCH, CORN; CROSCARMELLOSE SODIUM; HYPROMELLOSES; CELLULOSE, MICROCRYSTALLINE; MINERAL OIL; TITANIUM DIOXIDE

ASPIRIN FOR TIME CAP

ACTIVE INGREDIENT

Each tablet contains Aspirin 325 mg

INACTIVE INGREDIENT

corn starch, croscarmellose sodium, Hypromellose, microcrystalline cellulose, mineral oil, titanium dioxide

Ask a doctor before use if:
stomach bleeding warning applies to you
You have a history of stomach problems, such as heartburn
You have high blood pressure, heart disease, liver cirrhosis, or kidney disease
You are taking a diuretic
You have asthma
You have not been drinking fluids
You have lost a lot of fluid due to vomiting or diarrhea

WARNINGS

WARNINGS: Reye’s syndrome: Children and teenagers who have or are recovering from chicken pox or flu-like symptoms should not use this product. When using this product, if changes in behavior with nausea and vomiting occur, consult a doctor because these symptoms could be an early sign of Reye’s syndrome, a rare but serious illness.

Allergy alert: Aspirin may cause a severe allergic reaction, which may include, hives, facial swelling, shock, asthma (wheezing)

Stomach bleeding warning: This product contains an NSAID which may cause severe stomach bleeding. The chance is higher if you are age 60 or older, have had stomach ulcers or bleeding problems, take a blood thinning (anticoagulant) or steroid drug, take other drugs containing prescription or nonprescription NSAIDs (aspirin, ibuprofen, naproxen, or others); have 3 or more alcoholic drinks every day while using this product, take more or for a longer time than directed

Do not use

If you are allergic to aspirin or any other pain reliever/fever reducer

Directions:

Drink a full glass of water with each dose

Adults and children 12 years and over: take 1 to 2 tablets every 4 hours while symptoms last

Do not take more than 12 tablets in 24 hours unless directed by a doctor.

Children under 12 years: consult a doctor

KEEP OUT OF REACH OF CHILDREN

Keep out of the reach of children. In case of overdose, get medical help or contact a Poison Control Center right away.

PURPOSE

Pain Reliever

Uses:
For the temporary relief of minor aches and pains due to:
headache, colds, muscle pain, menstrual pain, toothache, minor pain of arthritis or as directed by your doctor.

Repackaged By :
Aidarex Pharmaceuticals LLC,
Corona, CA 92880